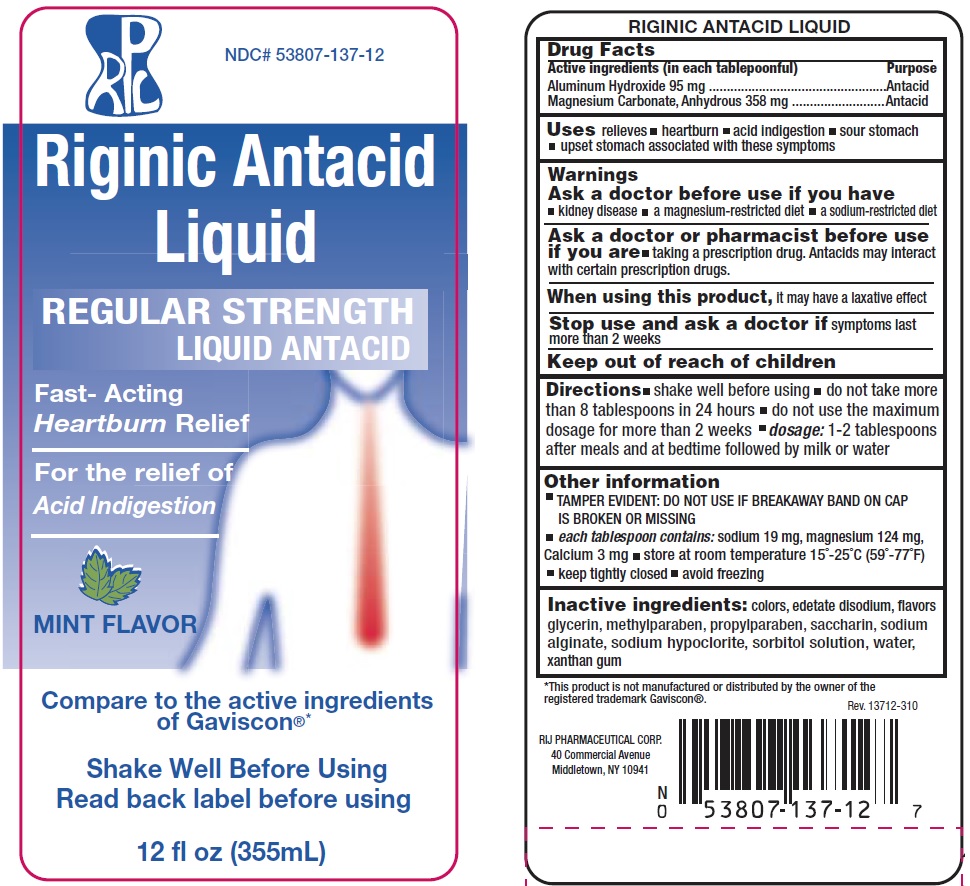 DRUG LABEL: Riginic Antacid Liquid
NDC: 53807-137 | Form: LIQUID
Manufacturer: Rij Pharmaceutical Corporation
Category: otc | Type: HUMAN OTC DRUG LABEL
Date: 20180430

ACTIVE INGREDIENTS: ALUMINUM HYDROXIDE 95 mg/15 mL; MAGNESIUM CARBONATE 358 mg/15 mL
INACTIVE INGREDIENTS: EDETATE DISODIUM; D&C YELLOW NO. 10; FD&C BLUE NO. 1; GLYCERIN; METHYLPARABEN; PROPYLPARABEN; SACCHARIN; SODIUM ALGINATE; SODIUM HYPOCHLORITE; SORBITOL; WATER; XANTHAN GUM

Drug Facts

Active ingredient (in each 15mL tablespoonful)

Aluminum Hydroxide 95mg

Magnesium Carbonate, Anhydrous 358mg

Purpose

Antacid

Uses

relieves

- heartburn
- acid indigestion
- sour stomach
- upset stomach associated with these symptoms

Warnings

Ask a doctor before use if you have

- kidney disease
- a magnesium-restricted diet
- a sodium-restricted diet

Ask a doctor or pharmacist before use if you are

- taking a prescription drug. Antacids may interact with certain prescription drugs.

When using this product,

- it may have a laxative effect

Stop use and ask a doctor if

symptoms last more than two weeks

Directions

- shake well before using
- do not take more than 8 tablespoons in 24 hours
- do not use the maximum dosage for more than 2 weeks
- dosage: 1-2 tablespoons after meals and at bedtime followed by milk or water

Other information

- TAMPER EVIDENT: DO NOT USE IF BREAKAWAY BAND ON CAP IS BROKEN OR MISSING
- each tablespoon contains: sodium 19 mg, magnesium 124 mg, calcium 3 mg
- Store at room temperature 15º - 25ºC (59º - 77ºF)
- keep tightly closed
- avoid freezing

Inactive ingredients

colors, edetate disodium, flavors, glycerin, methylparaben, propylparaben, saccharin, sodium alginate, sodium hypochlorite, sorbitol solution, water, xanthan gum